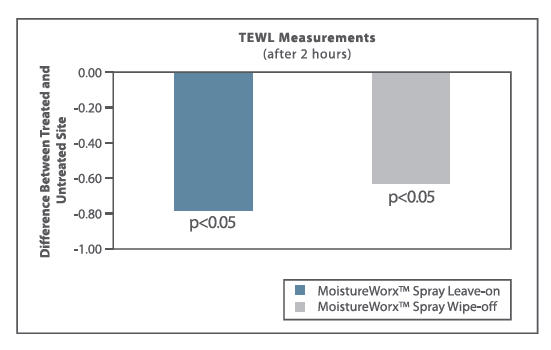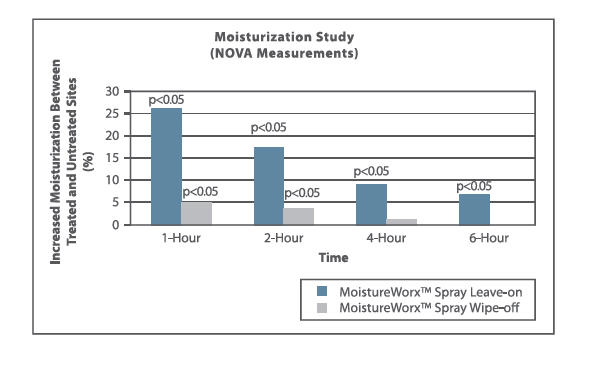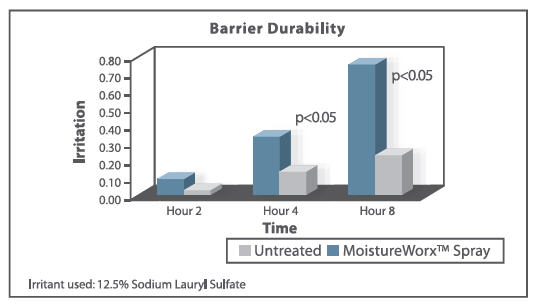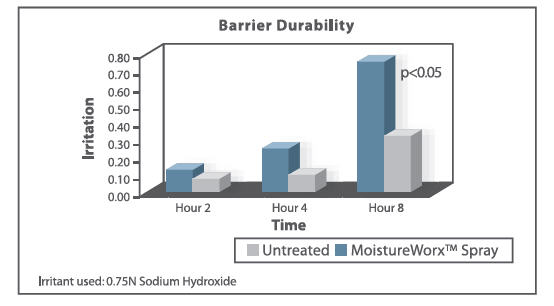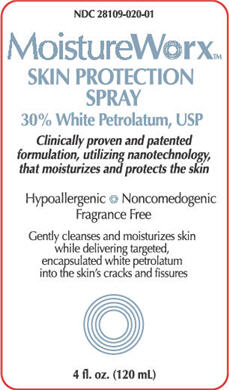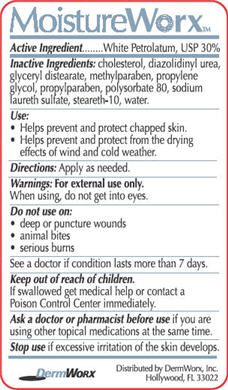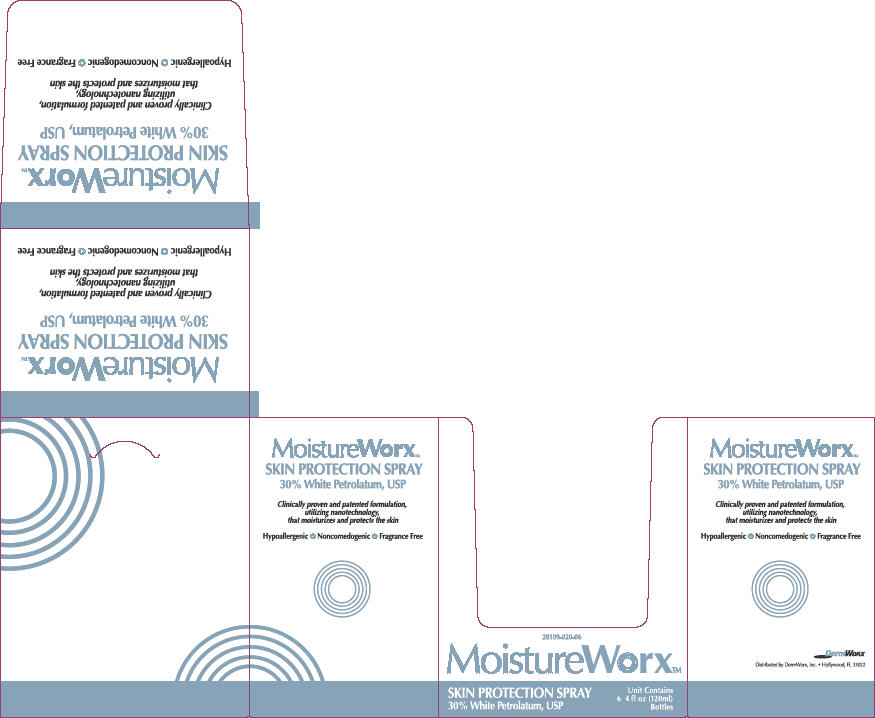 DRUG LABEL: MoistureWorx
NDC: 28109-020 | Form: SPRAY
Manufacturer: DermWorx Incorporated
Category: otc | Type: HUMAN OTC DRUG LABEL
Date: 20100216

ACTIVE INGREDIENTS: PETROLATUM 36 mL/120 mL

MoistureWorx™ Skin Protection Spray
(30% White Petrolatum)

Active ingredient

White Petrolatum, USP 30%

Inactive Ingredients

cholesterol, diazolidinyl urea, glyceryl distearate, methylparaben, propylene glycol, propylparaben, polysorbate 80, sodium laureth sulfate, steareth-10, water.

Use:

- Helps prevent and protect chapped skin.
- Helps prevent and protect from the drying effects of wind and cold weather.

Directions:

Apply as needed.

Warnings: For external use only.

When using, do not get into eyes.

Do not use on:

- deep or puncture wounds
- animal bites
- serious burns

See a doctor if condition lasts more than 7 days.

Keep out of reach of children.

If swallowed get medical help or contact a Poison Control Center immediately.

Ask a doctor or pharmacist before use

if you are using other topical medications at the same time.

Stop use

if excessive irritation of the skin develops.

Patient Information

MOISTUREWORX™

(White Petrolatum, USP - 30%) Spray

Active Ingredient:

White Petrolatum, USP 30%

Inactive Ingredients:

cholesterol, diazolidinyl urea, glyceryl distearate, methylparaben, propylene glycol, propylparaben, polysorbate 80, sodium laureth sulfate, steareth-10, water.

Use:

- Helps prevent and protect chapped or cracked skin.
- Helps prevent and protect from the drying effects of wind and cold weather.
- Helps prevent loss of moisture, keeping the skin smooth.

Clinical Pharmacology:

The outer layer of skin consists of dead skin cells which protect the delicate living cells of the deeper layers beneath. This outer layer needs to stay moisturized in order to protect the deeper layers of skin. To keep the moisture (water) from leaving the outer layer, your skin produces natural oils. These oils also help keep irritants from the deeper layers of skin.

Regular washing with soap, or exposure to chemicals, can remove these natural oils. When the natural oil is stripped from the outer layer, moisture quickly leaves the surface resulting in dry, irritated, and itchy skin. Worse, the deeper layers of skin are now left exposed to harsh damaging irritants such as detergents, powder, etc. This results in more dry, irritated, and itchy skin that ultimately becomes chapped, cracked and damaged.

Everyday skin lotions only attempt to replace natural oils with artificial ones. This is a temporary relief but does little to heal the skin. Regular use of these lotions can actually cause the skin to produce less natural oils. Instead of attempting to replace these natural oils, MoistureWorx™, when applied to the skin, forms a moisture-barrier with the outer layer of dead skin cells. Thus, MoistureWorx™ helps reduce the natural oil and moisture loss, allowing the skin to heal itself. MoistureWorx™ helps the outer layer of skin keep its natural oils and moisturizers that protect the deeper layers of skin, leaving skin soft and supple. MoistureWorx™ keeps the outer layer of skin functioning so it can breathe and perspire naturally.

The active ingredient in MoistureWorx™ is white petrolatum, one of the most common dermal barrier ingredients. Most white petrolatum-based products currently marketed by cosmetic and pharmaceutical companies are in a cream, lotion or ointment form. However, these products are thick, oily and aesthetically unpleasant. The occlusive nature and moisturizing properties are desirable, but the heavy, characteristic feel of white petrolatum is not.

The use of white petrolatum as an emollient has been well accepted for dry skin conditions, especially with flaking skin such as sunburn and chapping. It has been shown that when white petrolatum is applied to sunburned skin, evaporation is curtailed - it acts as a barrier to loss of moisture from the epidermis.

White petrolatum has a long history of consumer use, efficacy and safety. As a result, significant evidence of efficacy and safety exists from the universal use of white petrolatum over many decades for a wide variety of topical indications. Studies have shown that when large amounts of white petrolatum are ingested, the product is essentially nontoxic. It has even been approved as a direct food additive. Further, it has been established that white petrolatum is not absorbed through intact or injured skin and is neither sensitizing nor irritating.

As a result, clinical and marketing experience has confirmed that white petrolatum is safe when used as a skin protectorant. It has an extremely low risk in actual consumer use situations. Moreover, petroleum provides a favorable public health benefit, requires no specific dosage limitation, and requires few specific warnings and no general warnings (e.g. pregnancy or overdose).

The ease of application and delivery of white petrolatum over a relatively large surface area was a key consideration in developing MoistureWorx™. DermWorx has incorporated a novel microencapsulation technique (Novasome®) in the formulation that will significantly increase the aqueous solubility of white petrolatum. This technology utilizes proprietary organized lipid structures and lipid vesicle encapsulation technologies and provides for a nanoparticle in an aqueous transport system. Using this technology, high concentrations of thick solids such as white petrolatum can be transformed into water-based sprayable products.

To evaluate the moisturization efficacy of MoistureWorx™, a clinical study was performed in thirty-three (33) subjects ranging in age from 21 to 60 years with mild to moderate dry skin. MoistureWorx™ was applied two different ways, as a “leave-on” and as a “wipe-off” product.

Moisturization efficacy was determined via a measurement of the skin moisture content (DPM).

Trans-epidermal water loss (TEWL) was also determined.

The results show that MoistureWorx™ used either as a “leave-on” or as a “wipe-off” product, was effective in moisturizing the skin. In addition, the rate of moisture loss through the skin was significantly reduced.

The barrier durability of MoistureWorx™ in protecting the skin from irritation resulting from exposure to know irritants was also evaluated. Twenty-nine (29) subjects completed the study. Sodium lauryl sulfate at concentrations of 7.5%, 10.0% and 12.5% and sodium hydroxide at a concentration of 0.75N were applied to a small patch (8 mm in diameter) and the patches were applied to sites, treated and untreated, on each subjects back. The patches were removed at 2, 4 and 8 hours after application and the sites evaluated for dermal irritation due to the irritants.

The results show that MoistureWorx™ protected the skin exposed to the irritants after eight hours vs. unprotected skin.

Warnings:

For external use only.

When using this product:

- do not get into eyes.

Do not use on:

- deep or puncture wounds
- animal bites
- serious burns

See a doctor if condition lasts more than 7 days.

Directions:

Apply as needed not less than every four hours.

How Supplied:

4 fl. oz spray bottle

NDC: 28109-020-01

Distributed by:

DermWorx, Inc.
Hollywood, FL 33022
E-mail: info@dermworx.com
www.dermworx.com

Principal Display Panel - Bottle Label

NDC 28109-020-01

MoistureWorx™

SKIN PROTECTION SPRAY

30% White Petrolatum, USP

Clinically proven and patented formulation, utilizing nanotechnology, that moisturizes and protects the skin

Hypoallergenic • Noncomedogenic • Fragrance Free

Gently cleanses and moisturizes skin while delivering targeted, encapsulated white petrolatum into the skin's crack and fissures

4 fl. oz. (120 mL)

Bottle Label

Principal Display Panel - Outer Carton Label

MoistureWorx™

SKIN PROTECTION SPRAY

30% White Petrolatum, USP

Clinically proven and patented formulation, utilizing nanotechnology, that moisturizes and protects the skin

Hypoallergenic • Noncomedogenic • Fragrance Free

28109-020-06

MoistureWorx™

SKIN PROTECTION SPRAY

30% White Petrolatum, USP

Unit Contains 6 4fl oz (120mL) Bottles

Distributed by DermWorx, Inc. • Hollywood, FL 33022

Outer Carton Label